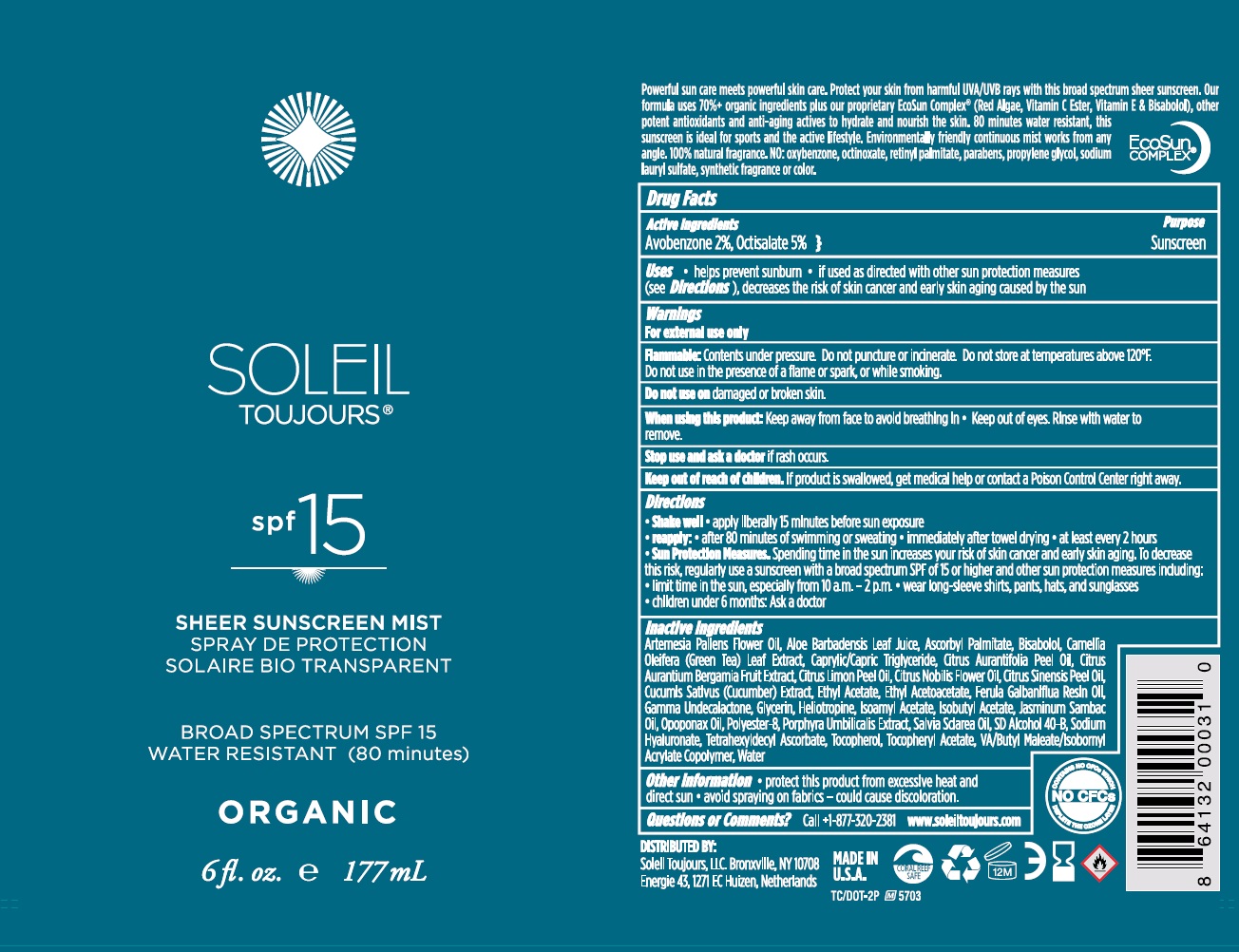 DRUG LABEL: Soleil Toujours
NDC: 13630-0133 | Form: SPRAY
Manufacturer: Prime Packaging Inc.
Category: otc | Type: HUMAN OTC DRUG LABEL
Date: 20200117

ACTIVE INGREDIENTS: AVOBENZONE 16.52 mg/1 mL; OCTISALATE 41.3 mg/1 mL
INACTIVE INGREDIENTS: ALOE VERA LEAF; ASCORBYL PALMITATE; LEVOMENOL; GALBANUM OIL; MEDIUM-CHAIN TRIGLYCERIDES; OPOPANAX RESIN; ORANGE OIL; BERGAMOT OIL; DAVANA OIL; WATER; ALCOHOL; .GAMMA.-UNDECALACTONE; PIPERONAL; ISOBUTYL ACETATE; GLYCERIN; ISOAMYL ACETATE; GREEN TEA LEAF; CUCUMBER JUICE; PORPHYRA UMBILICALIS; POLYESTER-8 (1400 MW, CYANODIPHENYLPROPENOYL CAPPED); HYALURONATE SODIUM; TETRAHEXYLDECYL ASCORBATE; .ALPHA.-TOCOPHEROL ACETATE; VINYL ACETATE; DIBUTYL MALEATE; ISOBORNYL ACRYLATE; TOCOPHEROL; CLARY SAGE OIL; ETHYL ACETOACETATE; LEMON OIL; LIME OIL; CITRUS NOBILIS; JASMINUM SAMBAC WHOLE; ETHYL ACETATE

Soleil Toujours SPF 15 Sheer Sunscreen Mist

Active Ingredients

Avobenzone 3%, Homosalate 7.5%, Octisalate 5%

Purpose

Sunscreen

Uses

- helps prevent sunburn • if used as directed with other sun protection measures (see Directions), decreases the risk of skin cancer and early skin aging caused by the sun

Warnings

For external use only

Flammable: Contents under pressure. Do not puncture or incinerate. Do not store at temperatures above 120ºF. Do not use in the presence of a flame or spark, or while smoking.

Do not useon damaged or broken skin.

When using this product: Keep away from face to avoid breathing in • Keep out of eyes. Rinse with water to remove.

Stop use and ask a doctor if rash occurs.

Keep out of reach of children. If product is swallowed, get medical help or contact a Poison Control Center right away.

Directions

- Shake well • apply liberally 15 minutes before sun exposure
- reapply: • after 80 minutes of swimming and sweating • immediately after towel drying • at least every 2 hours
- Sun Protection Measures. Spending time in the sun increases your risk of skin cancer and early skin aging. To decrease this risk, regularly use a sunscreen with a broad spectrum SPF of 15 or higher and other sun protection measures including: • limit time in the sun, especially from 10 a.m. - 2 p.m. • wear long-sleeve shirts, pants, hats, and sunglasses • children under 6 months: Ask a doctor

Inactive ingredients

Artemesia Pallens Flower Oil, Aloe Barbadensis Leaf Juice, Ascorbyl Palmitate, Bisabolol, Camellia Oleifera (Green Tea) Leaf Extract, Caprylic/Capric Triglyceride, Citrus Aurantifolia Peel Oil, Citrus Aurantium Bergamia Fruit Extract, Citrus Limon Peel Oil, Citrus Nobilis Flower Oil, Citrus Sinensis Peel Oil, Cucumis Sativus (Cucumber) Extract, Ethyl Acetate, Ethyl Acetoacetate, Ferula Galbaniflua Resin Oil, Gamma Undecalactone, Glycerin, Heliotropine, Isoamyl Acetate, Isobutyl Acetate, Jasminum Sambac Oil, Opoponax Oil, Polyester-8, Porphyra Umbilicalis Extract, Salvia Sclarea Oil, SD Alcohol 40-B, Sodium Hyaluronate, Tetrahexyldecyl Ascorbate, Tocopherol, Tocopheryl Acetate, VA/Butyl Maleate/Isobornyl Acrylate Copolymer, Water

Other information

- protect this product from excessive heat and direct sun • avoid spraying on fabrics - could cause discoloration.

Question or comments?

Call +1-877-320-2381 www.soleiltoujours.com